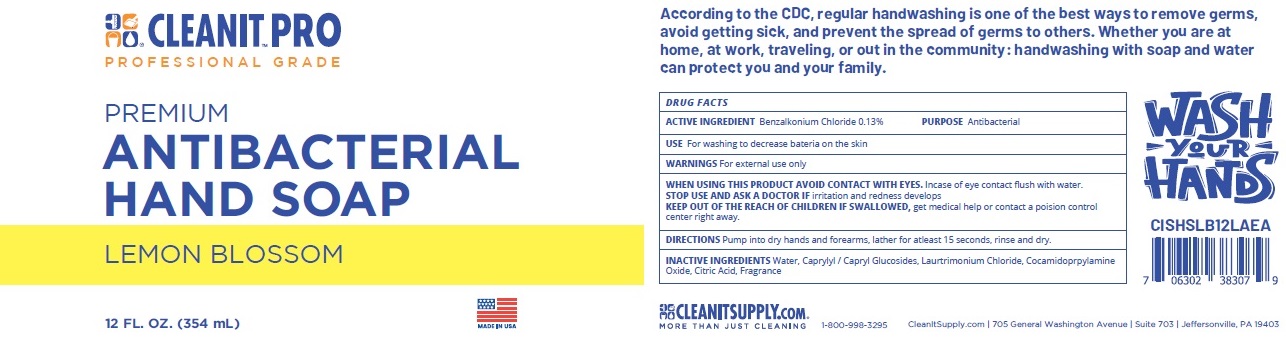 DRUG LABEL: Premium Antibacterial Hand
NDC: 74811-002 | Form: SOAP
Manufacturer: Insolcorp, LLC
Category: otc | Type: HUMAN OTC DRUG LABEL
Date: 20201210

ACTIVE INGREDIENTS: BENZALKONIUM CHLORIDE 1.3 mg/1 mL
INACTIVE INGREDIENTS: WATER; DECYL GLUCOSIDE; LAURTRIMONIUM CHLORIDE; COCAMIDOPROPYLAMINE OXIDE; CITRIC ACID MONOHYDRATE

Premium Antibacterial Hand Soap

ACTIVE INGREDIENT

Benzalkonium Chloride 0.13%

PURPOSE

Antibacterial

USE

For washing to decrease bacteria on the skin

WARNINGS

For external use only

WHEN USING THIS PRODUCT AVOID CONTACT WITH EYES. Incase of eye contact flush with water.

STOP USE AND ASK A DOCTOR IF irritation and redness develops

KEEP OUT OF REACH OF CHILDREN

KEEP OUT OF THE REACH OF CHILDREN IF SWALLOWED, get medical help or contact a poision control
center right away.

DIRECTIONS

Pump into dry hands and forearms, lather for atleast 15 seconds, rinse and dry.

INACTIVE INGREDIENTS

Water, Caprylyl / Capryl Glucosides, Laurtrimonium Chloride, Cocamidoprpylamine Oxide, Citric Acid, Fragrance

PRINCIPAL DISPLAY PANEL

PREMIUM ANTIBACTERIAL HAND SOAP

LEMON BLOSSOM

12 FL. OZ. (354 mL)